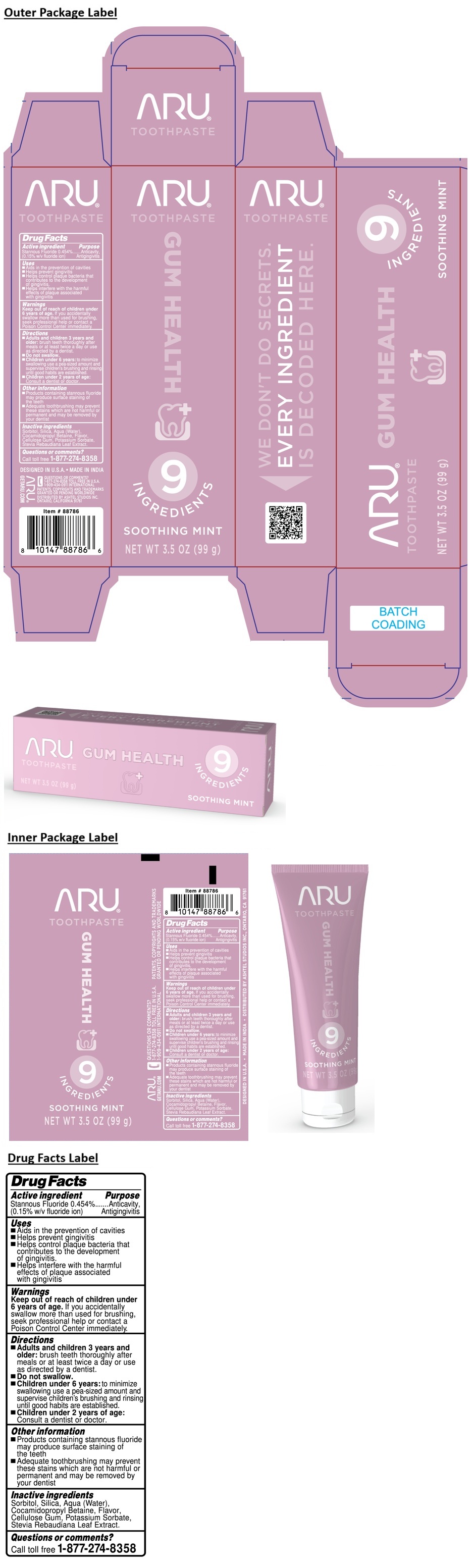 DRUG LABEL: ARU GUM HEALTH
NDC: 70108-288 | Form: PASTE, DENTIFRICE
Manufacturer: Ashtel Studios, Inc.
Category: otc | Type: HUMAN OTC DRUG LABEL
Date: 20260130

ACTIVE INGREDIENTS: STANNOUS FLUORIDE 0.11 g/100 g
INACTIVE INGREDIENTS: SORBITOL; SILICON DIOXIDE; WATER; COCAMIDOPROPYL BETAINE; CARBOXYMETHYLCELLULOSE SODIUM, UNSPECIFIED; POTASSIUM SORBATE; STEVIA REBAUDIANA LEAF

ARU® TOOTHPASTE GUM HEALTH

Active ingredient

Stannous Fluoride 0.454%
(0.15% w/v fluoride ion)

Purpose

Anticavity, Antigingivitis

Uses

- Aids in the prevention of cavities
- Helps prevent gingivitis
- Helps control plaque bacteria that contributes to the development of gingivitis.
- Helps interfere with the harmful effects of plaque associated with gingivitis

Warnings

Keep out of reach of children under 6 years of age. If you accidentally swallow more than used for brushing, seek professional help or contact a Poison Control Center immediately.

Directions

- Adults and children 3 years and older: brush teeth thoroughly after meals or at least twice a day or use as directed by a dentist.
- Do not swallow.
- Children under 6 years: to minimize swallowing use a pea-sized amount and supervise children's brushing and rinsing until good habits are established.
- Children under 2 years of age: Consult a dentist or doctor.

Other information

- Products containing stannous fluoride may produce surface staining of the teeth
- Adequate toothbrushing may prevent these stains which are not harmful or permanent and may be removed by your dentist

Inactive ingredients

Sorbitol, Silica, Aqua (Water), Cocamidopropyl Betaine, Flavor, Cellulose Gum, Potassium Sorbate, Stevia Rebaudiana Leaf Extract.

Questions or comments?

Call toll free 1-877-274-8358

9 INGREDIENTS

SOOTHING MINT

WE DON'T DO SECRETS.

EVERY INGREDIENT IS DECODED HERE.

DESIGNED IN U.S.A. • MADE IN INDIA

GETARU.COM

1-909-434-0911 INTERNATIONAL

PATENTS, COPYRIGHTS AND TRADEMARKS GRANTED OR PENDING WORLDWIDE

DISTRIBUTED BY ASHTEL STUDIOS INC.
ONTARIO, CALIFORNIA 91761